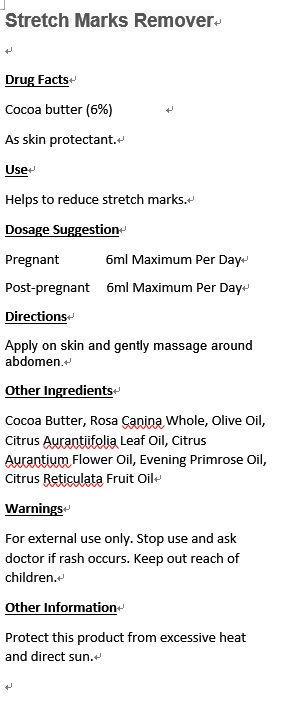 DRUG LABEL: Atopic Healer Synergy
NDC: 70470-1013 | Form: OIL
Manufacturer: PHYTOPIA CO., LTD.
Category: otc | Type: HUMAN OTC DRUG LABEL
Date: 20161024

ACTIVE INGREDIENTS: BALSAM PERU OIL 3.6 mg/50 mL; COCOA BUTTER 4.9 mg/50 mL
INACTIVE INGREDIENTS: EVENING PRIMROSE OIL; BERGAMOT OIL; TANSY OIL; HELICHRYSUM ITALICUM FLOWER OIL; OLIVE OIL; TAMANU OIL

Drug Facts

Cocoa butter (6%)

As skin protectant.

Use

Helps to reduce stretch marks.

Dosage Suggestion

Pregnant 6ml Maximum Per Day

Post-pragnant 6ml Maximum Per Day

Directions

Apply on skin and gentlely massage around abdomen.

INACTIVE INGREDIENT

Other Ingredients

Rosa Canina Whole, Olive Oil, Citrus Aurantiifolia Leaf Oil, Citrus Aurantium Flower Oil, Evening Primrose Oil, Citrus Reticulata Fruit Oil

Warnings

For external use only. Stop use and ask doctor if rash occurs. Keep out reach of children.

Other Information

Protect this product from excessive heat and direct sun.

Warnings

For external use only. Stop use and ask doctor if rash occurs. Keep out reach of children.

Stretch Marks Remover